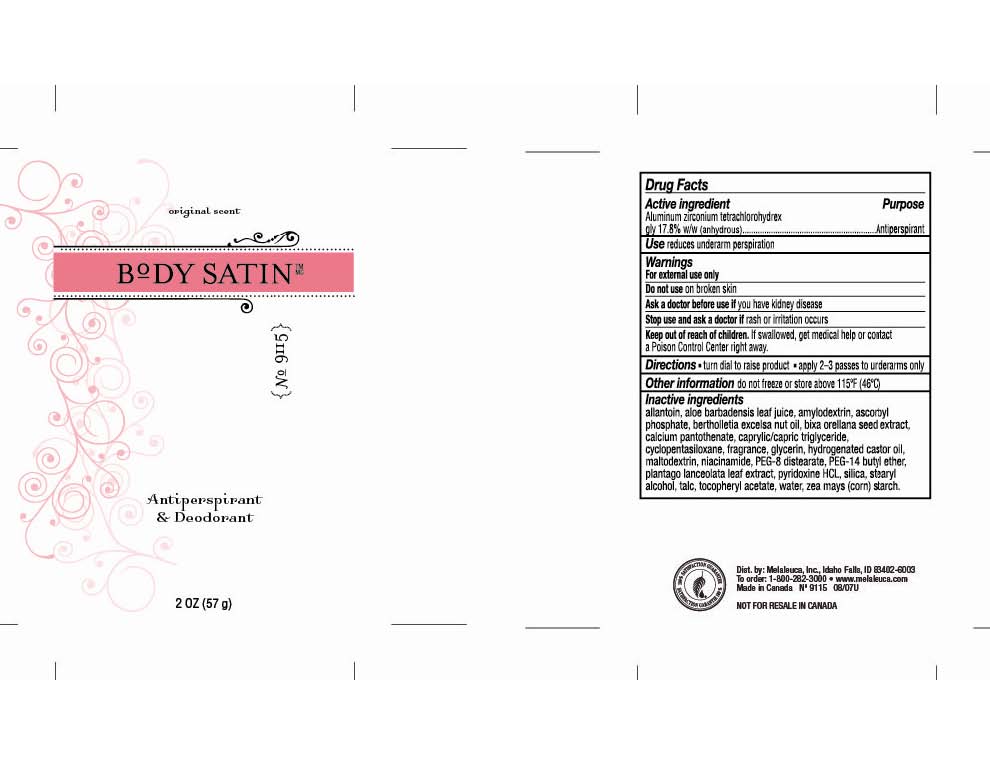 DRUG LABEL: Body Satin
NDC: 54473-152 | Form: STICK
Manufacturer: Melaleuca, Inc.
Category: otc | Type: HUMAN OTC DRUG LABEL
Date: 20110119

ACTIVE INGREDIENTS: ALUMINUM ZIRCONIUM TETRACHLOROHYDREX GLY 10.146 g/57 g
INACTIVE INGREDIENTS: ALLANTOIN; ALOE VERA LEAF; SODIUM ASCORBYL PHOSPHATE; BRAZIL NUT OIL; BIXA ORELLANA SEED; CALCIUM PANTOTHENATE; MEDIUM-CHAIN TRIGLYCERIDES; Cyclomethicone 5; GLYCERIN; HYDROGENATED CASTOR OIL; MALTODEXTRIN; NIACINAMIDE; PEG-8 DISTEARATE; PPG-14 BUTYL ETHER; PLANTAGO LANCEOLATA LEAF; PYRIDOXINE HYDROCHLORIDE; SILICON DIOXIDE; STEARYL ALCOHOL; Talc; ALPHA-TOCOPHEROL ACETATE; WATER; STARCH, CORN

Body Satin Antiperspirant & Deodorant Content of Label

Active ingredient
Aluminum zirconium tetrachlorohydrex gly 17.8%

Purpose
Antiperspirant

INDICATIONS AND USAGE

Use reduces underarm perspiration

Warnings
For external use only

Do not use on broken skin

Ask a doctor before use if you have kidney disease

Stop use and ask a doctor if rash or irritation occurs

Keep out of reach of children. If swallowed, get medical help or contact a Poison Control Center right away.

Directions

- turn dial to raise product
- apply 2 - 3 passes to underarms only

Other information do not freeze or store above 115°F (46°C)

Inactive ingredients
allantoin, aloe barbadensis leaf juice, amylodextrin, ascorbyl phosphate, bertholletia excelsa nut oil, bixa orellana seed extract, calcium pantothenate, caprylic/capric triglyceride, cyclopentasiloxane, fragrance, glycerin, hydrogenated castor oil, maltodextrin, niacinamide, PEG-8 distearate, PEG-14 butyl ether, plantago lanceolata leaf extract, pyridoxine HCL, silica, stearyl alcohol, talc, tocopheryl acetate, water, zea mays (corn) starch.